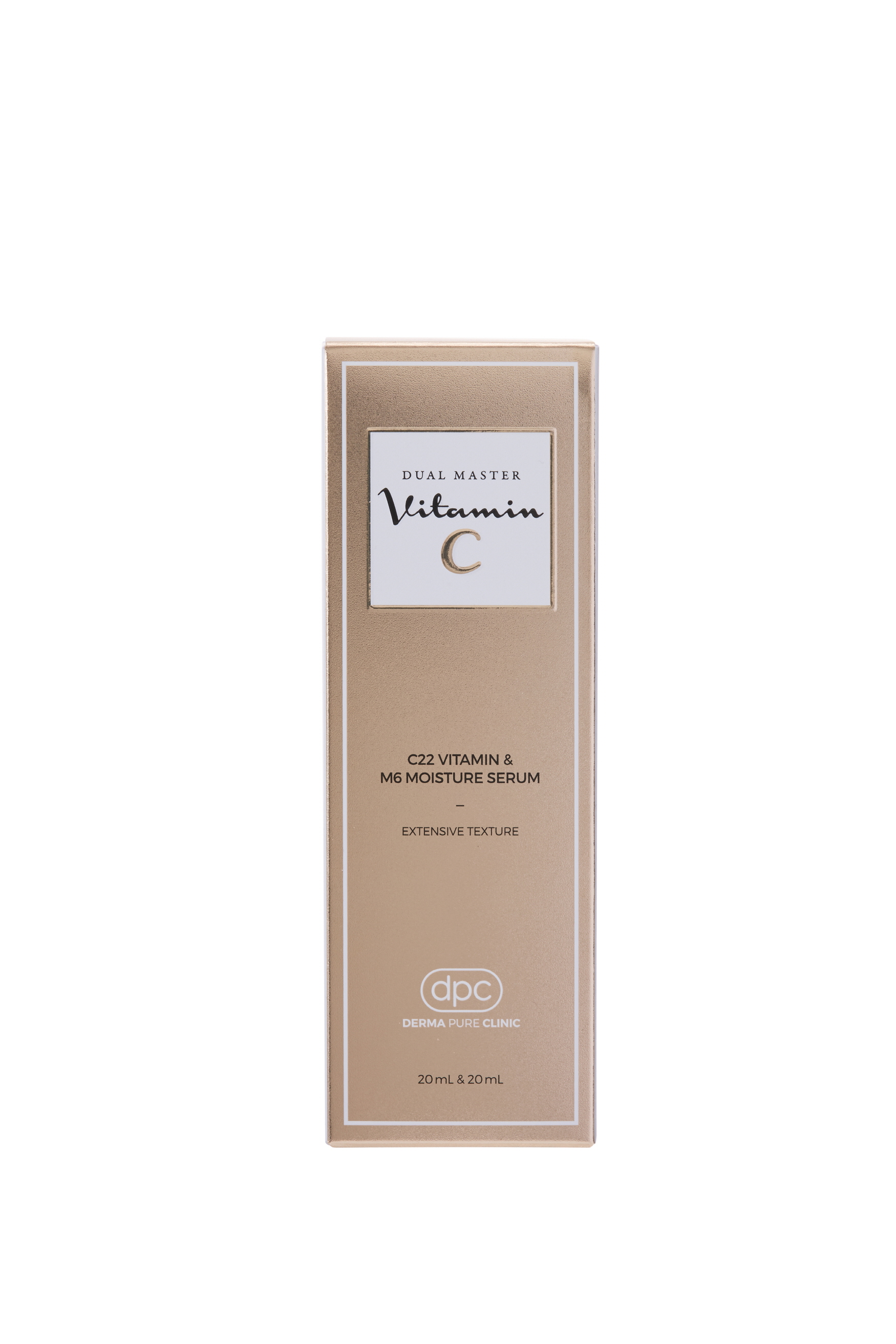 DRUG LABEL: DPC Dual Master Vitamin C
NDC: 71673-0005 | Form: LIQUID
Manufacturer: MSCO
Category: otc | Type: HUMAN OTC DRUG LABEL
Date: 20170823

ACTIVE INGREDIENTS: ADENOSINE 0.04 g/100 mL; NIACINAMIDE 2 g/100 mL
INACTIVE INGREDIENTS: WATER; HYALURONATE SODIUM; GLYCERIN

Drug Facts

ACTIVE INGREDIENT

NIACINAMIDE, ADENOSINE

INACTIVE INGREDIENT

Prunus Mume Flower Water
Hyaluronic Acid
Butylene Glycol
Water
Theanine
Milk Lipids
Glutathione
Hydrogenated Lecithin
Ceramide NP
1,2-Hexanediol
Glycerin
Panthenol
Propanediol
Benzyl Glycol
Ethylhexylglycerin
Raspberry Ketone
Hydrolyzed Hyaluronic Acid
Sodium Hyaluronate
Sodium Hyaluronate Crosspolymer
Lactococcus Ferment Lysate
Sodium Benzoate
Hydrogenated Lecithin
Polyglycerin-3
PCA
PEG-240/HDI Copolymer Bis-Decyltetradeceth-20 Ether
Malus Domestica Fruit Cell Culture Extract
Caprylyl Glycol
Tropolone
Octyldodeceth-16
Arginine
Sodium Acetylated Hyaluronate
Hydrolyzed Glycosaminoglycans
Citric Acid
Tremella Fuciformis Polysaccharide
Tuber Melanosporum Extract
Astragalus Membranaceus Root Extract
Rhizobian Gum
Copper PCA
Dipotassium Glycyrrhizate
Betaine
Acetyl Hexapeptide-8
PVP
Fullerenes
Fragrance

PURPOSE

Anti-Wrinkle

Whitening

keep out of reach of the children

INDICATIONS AND USAGE

Apply a proper amount on the skin and spread evenly.

WARNINGS

For external use only.
Avoid contact with eyes. Not for human consumption.
Discontinue use if irritation occurs.
If irritation persists, consult a physician.

DOSAGE AND ADMINISTRATION

for external use only